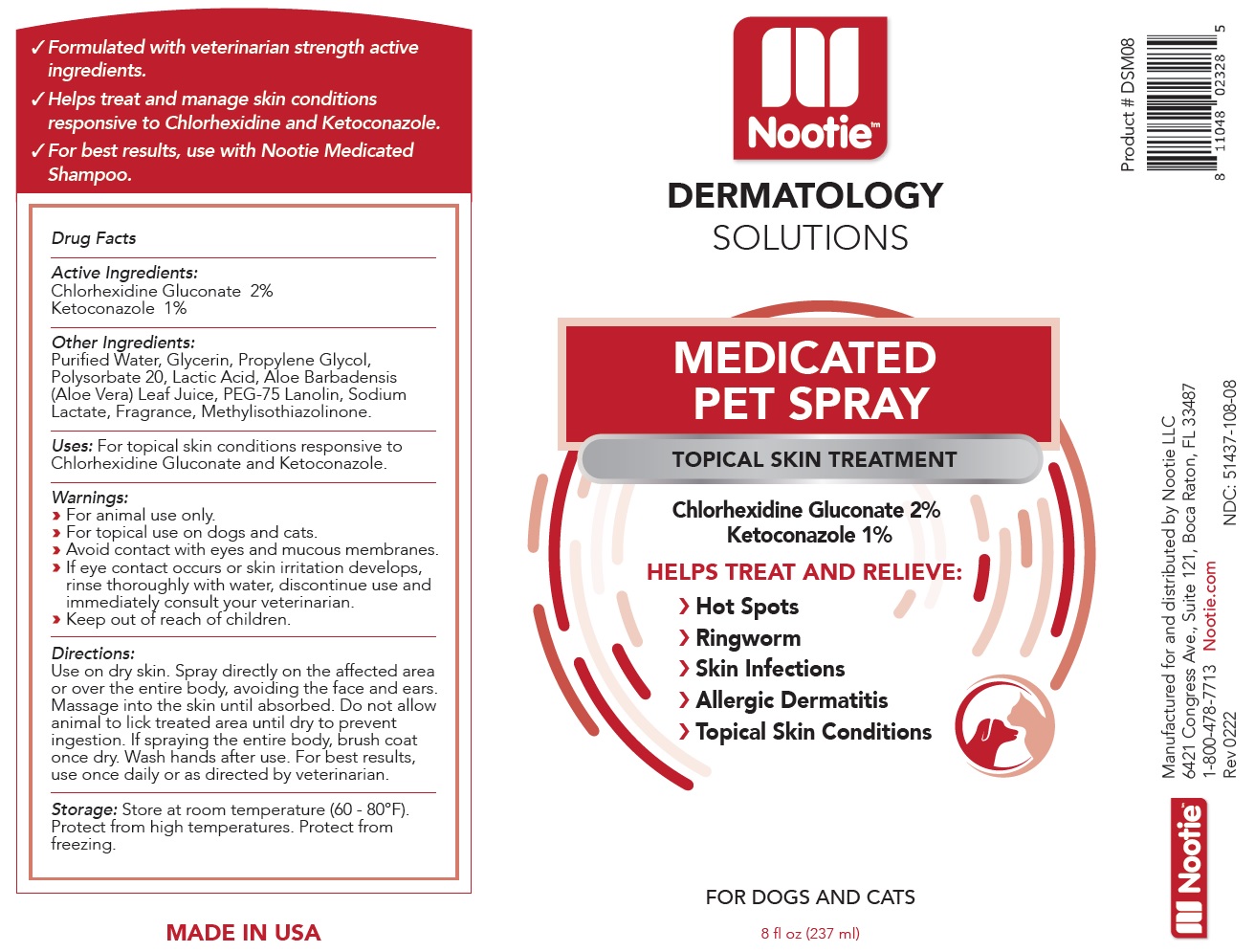 DRUG LABEL: Nootie Medicated Pet
NDC: 51437-108 | Form: SPRAY
Manufacturer: Nootie LLC
Category: animal | Type: OTC ANIMAL DRUG LABEL
Date: 20221124

ACTIVE INGREDIENTS: CHLORHEXIDINE GLUCONATE 20 mg/1 mL; KETOCONAZOLE 10 mg/1 mL
INACTIVE INGREDIENTS: WATER; GLYCERIN; PROPYLENE GLYCOL; POLYSORBATE 20; LACTIC ACID, UNSPECIFIED FORM; ALOE VERA LEAF; PEG-75 LANOLIN; SODIUM LACTATE; METHYLISOTHIAZOLINONE

Nootie™ MEDICATED PET SPRAY

Active Ingredients:

Chlorhexidine Gluconate 2%
Ketoconazole 1%

Other Ingredients:

Purified Water, Glycerin, Propylene Glycol, Polysorbate 20, Lactic Acid, Aloe Barbadensis (Aloe Vera) Leaf Juice, PEG-75 Lanolin, Sodium Lactate, Fragrance, Methylisothiazolinone.

Uses:

For topical skin conditions responsive to Chlorhexidine Gluconate and Ketoconazole.

Warnings:

› For animal use only.
› For topical use on dogs and cats.
› Avoid contact with eyes and mucous membranes.
› If eye contact occurs or skin irritation develops, rinse thoroughly with water, discontinue use and immediately consult your veterinarian.
› Keep out of reach of children.

Directions:

Use on dry skin. Spray directly on the affected area or over the entire body, avoiding the face and ears. Massage into the skin until absorbed. Do not allow animal to lick treated area until dry to prevent ingestion. If spraying the entire body, brush coat once dry. Wash hands after use. For best results, use once daily or as directed by veterinarian.

Storage:

Store at room temperature (60 - 80°F). Protect from high temperatures. Protect from freezing.

Nootie™ DERMATOLOGY SOLUTIONS

TOPICAL SKIN TREATMENT

HELPS TREAT AND RELIEVE:
› Hot Spots
› Ringworm
› Skin Infections
› Allergic Dermatitis
› Topical Skin Conditions

FOR DOGS AND CATS

√ Formulated with veterinarian strength active ingredients.
√ Helps treat and manage skin conditions responsive to Chlorhexidine and Ketoconazole.
√ For best results, use with Nootie Medicated Shampoo.

MADE IN USA

Manufactured for and distributed by Nootie LLC
6421 Congress Ave., Suite 121, Boca Raton, FL 33487
1-800-478-7713 Nootie.com